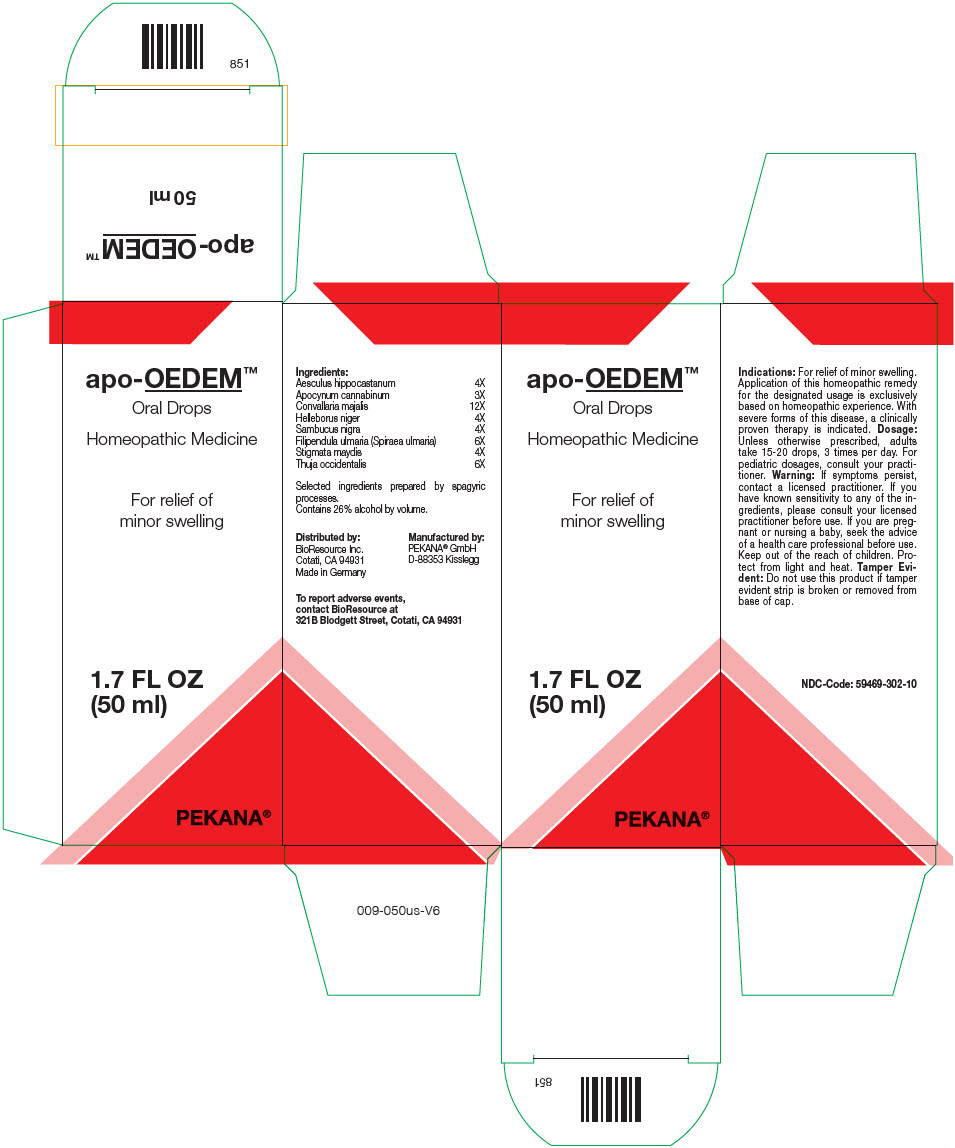 DRUG LABEL: apo-OEDEM
NDC: 59469-302 | Form: SOLUTION/ DROPS
Manufacturer: PEKANA Naturheilmittel Gmbh
Category: homeopathic | Type: HUMAN OTC DRUG LABEL
Date: 20230111

ACTIVE INGREDIENTS: HORSE CHESTNUT 4 [hp_X]/50 mL; APOCYNUM CANNABINUM ROOT 3 [hp_X]/50 mL; CONVALLARIA MAJALIS FLOWERING TOP 12 [hp_X]/50 mL; HELLEBORUS NIGER ROOT 4 [hp_X]/50 mL; THUJA OCCIDENTALIS LEAFY TWIG 6 [hp_X]/50 mL; SAMBUCUS NIGRA FLOWERING TOP 4 [hp_X]/50 mL; FILIPENDULA ULMARIA ROOT 6 [hp_X]/50 mL; CORN SILK 4 [hp_X]/50 mL
INACTIVE INGREDIENTS: WATER; ALCOHOL

apo-OEDEM™

ACTIVE INGREDIENT

Ingredients:
Aesculus hippocastanum | 4X
Apocynum cannabinum | 3X
Convallaria majalis | 12X
Helleborus niger | 4X
Sambucus nigra | 4X
Filipendula ulmaria (Spiraea ulmaria) | 6X
Stigmata maydis | 4X
Thuja occidentalis | 6X

Selected ingredients prepared by spagyric processes.

INACTIVE INGREDIENT

Contains 26% alcohol by volume.

Indications

PURPOSE

For relief of minor swelling. Application of this homeopathic remedy for the designated usage is exclusively based on homeopathic experience. With severe forms of this disease, a clinically proven therapy is indicated.

Dosage

Unless otherwise prescribed, adults take 15-20 drops, 3 times per day. For pediatric dosages, consult your practitioner.

Warning

If symptoms persist, contact a licensed practitioner. If you have known sensitivity to any of the ingredients, please consult your licensed practitioner before use. If you are pregnant or nursing a baby, seek the advice of a health care professional before use.

Keep out of the reach of children.

STORAGE AND HANDLING

Protect from light and heat.

Tamper Evident

Do not use this product if tamper evident strip is broken or removed from base of cap.

QUESTIONS

To report adverse events, contact BioResource at 321B Blodgett Street, Cotati, CA 94931

Distributed by:
BioResource Inc.
Cotati, CA 94931

Manufactured by:
PEKANA® GmbH
D-88353 Kisslegg

PRINCIPAL DISPLAY PANEL - 50 ml Bottle Box

apo-OEDEM™

Oral Drops

Homeopathic Medicine

For relief of
minor swelling

1.7 FL OZ
(50 ml)

PEKANA®